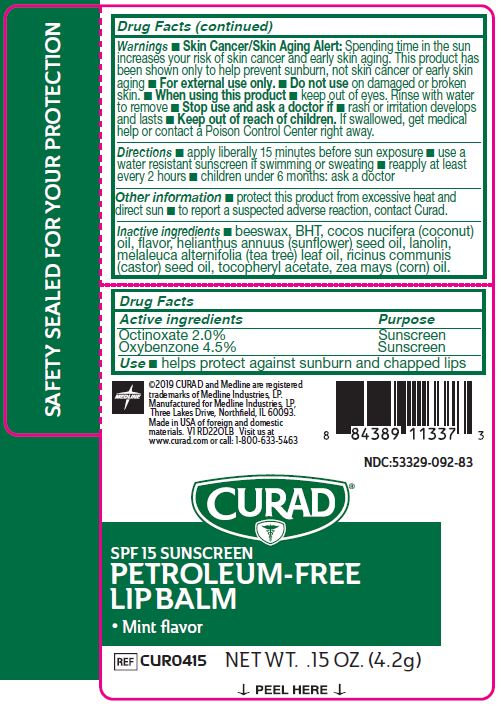 DRUG LABEL: Petroleum-Free Lip Balm
NDC: 53329-092 | Form: LIPSTICK
Manufacturer: Medline Industries, LP
Category: otc | Type: HUMAN OTC DRUG LABEL
Date: 20251009

ACTIVE INGREDIENTS: OCTINOXATE 2 g/100 g; OXYBENZONE 4.5 g/100 g
INACTIVE INGREDIENTS: YELLOW WAX; SUNFLOWER OIL; CASTOR OIL; LANOLIN; COCONUT OIL; CORN OIL; BUTYLATED HYDROXYTOLUENE; ALPHA-TOCOPHEROL ACETATE; TEA TREE OIL

092 Curad Petroleum-Free Lip Balm

Active ingredients

Octinoxate 2.0%

Oxybenzone 4.5%

Purpose

Sunscreen

Sunscreen

Use

- helps protect against sunburn and chapped lips

Warnings

- Skin Cancer/Skin Aging Alert: Spending time in the sun increases your risk of skin cancer and early skin aging. This product has been shown only to help prevent sunburn, not skin cancer or early skin aging.

- For external use only.

Do not use

on damaged or broken skin.

When using this product

- keep out of eyes. Rinse with water to remove

Stop use and ask a doctor if

- rash or irritation develops and lasts

Keep out of reach of children.

If swallowed, get medical help of contact a Poison Control Center right away.

Directions

- apply liberally 15 minutes before sun exposure
- use a water resistant sunscreen if swimming or sweating
- reapply at least every 2 hours
- children under 6 months: ask a doctor

Other Information

- protect this product from excessive heat and direct sun
- to report a suspected adverse reaction, contact Curad.

Inactive ingredients

beeswax, BHT, cocos nucifera (coconut) oil, flavor, helianthus annuus (sunflower) seed oil, lanolin, melaleuca alternifolia (tea tree) leaf oil, ricinus communis (castor) seed oil, tocopheryl acetate, zea mays (corn) oil.

Manufacturing Information

Manufactured for:

Medline Industries, LP

Three Lakes Drive, Northfield, IL 60093 USA

Made in USA of foreign and domestic materials

www.curad.com

1-800-633-5463

REF: CUR0415

V1 RD22OLB

RECENT MAJOR CHANGES

- Indications and Usage